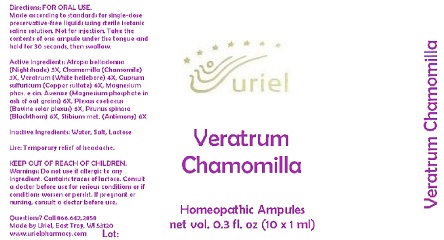 DRUG LABEL: Veratrum Chamomilla
NDC: 48951-9037 | Form: LIQUID
Manufacturer: Uriel Pharmacy Inc.
Category: homeopathic | Type: HUMAN OTC DRUG LABEL
Date: 20170815

ACTIVE INGREDIENTS: ATROPA BELLADONNA 3 [hp_X]/1 mL; MATRICARIA RECUTITA 3 1/1 mL; VERATRUM ALBUM ROOT 4 [hp_X]/1 mL; CUPRIC SULFATE 6 [hp_X]/1 mL; MAGNESIUM PHOSPHATE, TRIBASIC, PENTAHYDRATE 6 [hp_X]/1 mL; BOS TAURUS NERVE 6 [hp_X]/1 mL; PRUNUS SPINOSA FLOWER BUD 6 [hp_X]/1 mL; ANTIMONY 6 [hp_X]/1 mL
INACTIVE INGREDIENTS: WATER; SODIUM CHLORIDE; LACTOSE

Veratrum Chamomilla

INDICATIONS AND USAGE

Directions: FOR ORAL USE.

DOSAGE AND ADMINISTRATION

Take the contents of one ampule under the tongue and hold for 30 seconds, then swallow.

ACTIVE INGREDIENT

Active Ingredients: Atropa belladonna (Nightshade) 3X, Chamomilla (Chamomile) 3X, Veratrum (White hellebore) 4X, Cuprum sulfuricum (Copper sulfate) 6X, Magnesium phos. e cin. Avenae (Magnesium phosphate in ash of oat grains) 6X, Plexus coeliacus (Bovine solar plexus) 6X, Prunus spinosa (Blackthorn) 6X, Stibium met. (Antimony) 6X

Inactive Ingredients: Water, Salt, Lactose

PURPOSE

Use: Temporary relief of headache.

KEEP OUT OF REACH OF CHILDREN.

WARNINGS

Warnings: Do not use if allergic to any ingredient. Contains traces of lactose. Consult a doctor before use for serious conditions or if conditions worsen or persist. If pregnant or nursing, consult a doctor before use.

QUESTIONS

Questions? Call 866.642.2858 Made by Uriel, East Troy, WI 53120 www.urielpharmacy.com